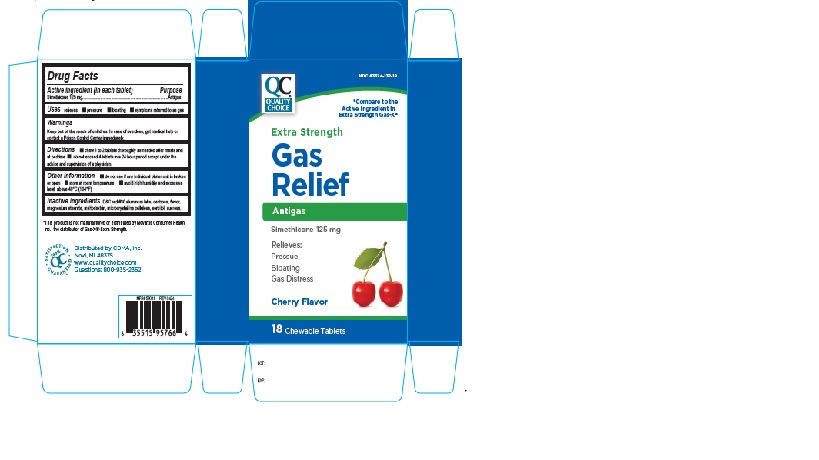 DRUG LABEL: QCH Extra Strength Gas Relief Cherry Flavor 134CHR
NDC: 83324-132 | Form: TABLET, CHEWABLE
Manufacturer: Chain Drug Marketing Association Inc.
Category: otc | Type: Human OTC Drug Label
Date: 20240827

ACTIVE INGREDIENTS: DIMETHICONE 125 mg/1 1
INACTIVE INGREDIENTS: D&C RED NO. 30 ALUMINUM LAKE; MAGNESIUM STEARATE; CELLULOSE, MICROCRYSTALLINE; SORBITOL; SUCROSE; MALTODEXTRIN; DEXTROSE, UNSPECIFIED FORM

QCH extra strength Gas Relief 134CHR

ACTIVE INGREDIENT(S)

Simethicone 125 mg

PURPOSE

Anti-gas

USE(S)

relieves:

- Pressure
- bloating
- Symptoms referred to as gas

WARNINGS

.

KEEP OUT OF THE REACH OF CHILDREN.

In case of overdose, get medical help or contact a poison Control Centre immediately.

DIRECTIONS

- chew 1 to 2 tablets thoroughly as needed after meals and at bedtime
- do not exceed 4 tablets in a 24 hour period except under the advice and supervision of a physician.

OTHER INFORMATION

- do not use if any individual blister unit is broken or open
- store at room temperature
- avoid high humidity and excessive heat, above 40ºC (104ºF)

INACTIVE INGREDIENTS

D&C red #30 aluminum lake, dextrose, flavor, magnesium stearate, maltodextrin, microcrystalline cellulose, sorbitol, sucrose.

PRINCIPAL DISPLAY PANEL

NDC 83324-132-18

QC

QUALITY CHOICE

*Compare to the Active ingredient in Extra Strength Gas-X®

Extra Strength

Gas Relief

Antigas

Simethicone 125 mg

Relieves:

Pressure

Bloating

Gas Distress

cherry Flavor

18 chewable tablets